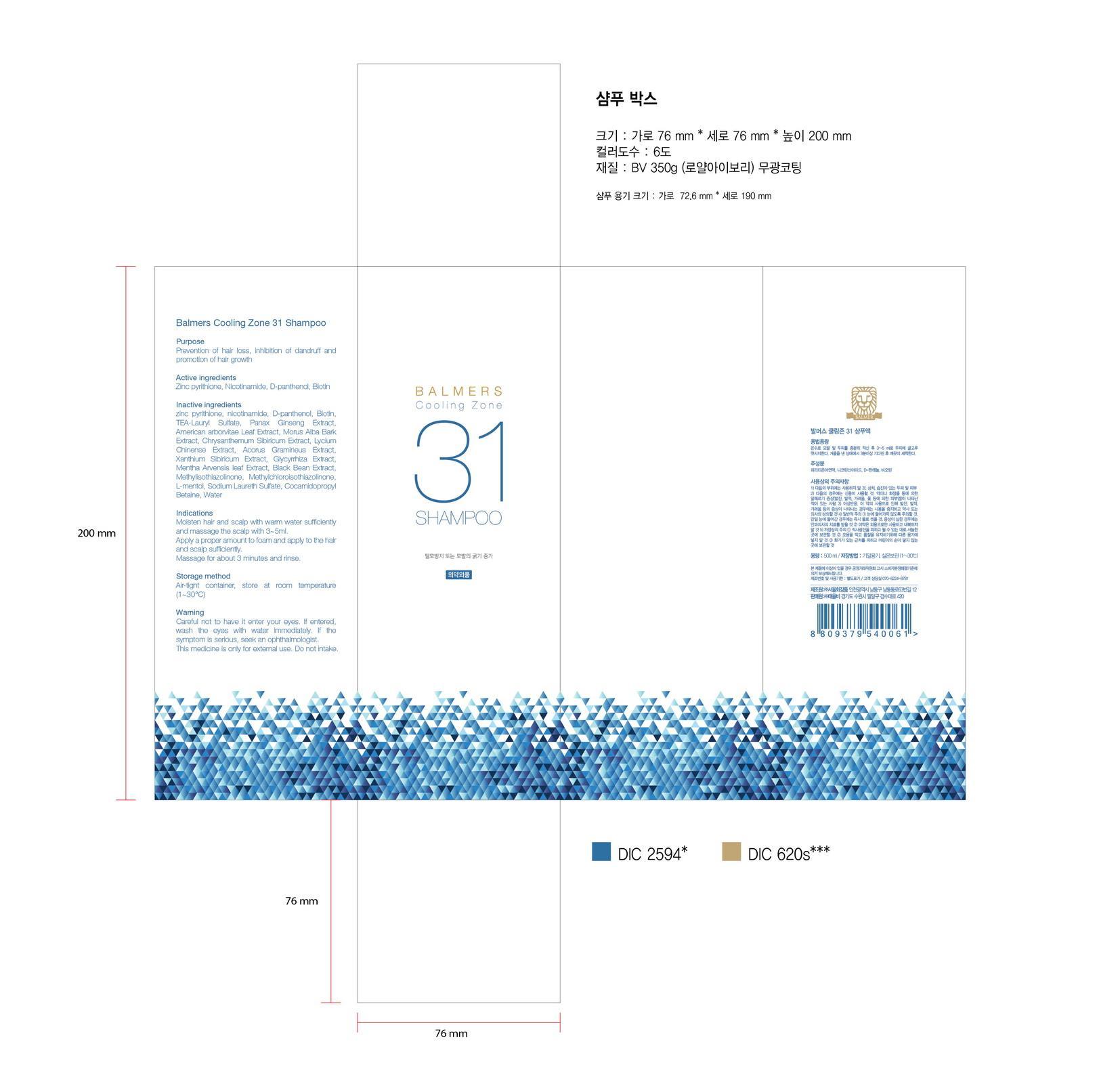 DRUG LABEL: Balmers Cooling Zone 31
NDC: 69927-001 | Form: SHAMPOO
Manufacturer: Tae Eul Bi Co., Ltd.
Category: otc | Type: HUMAN OTC DRUG LABEL
Date: 20150720

ACTIVE INGREDIENTS: PYRITHIONE ZINC 1.05 g/100 mL
INACTIVE INGREDIENTS: WATER; BIOTIN

Drug Facts

ACTIVE INGREDIENT

zinc pyrithione

INACTIVE INGREDIENT

water, nicotinamide, d-panthenol, biotin, l-menthol, etc.

PURPOSE

scalp protectant

keep out or reach of the children

INDICATIONS AND USAGE

-Moisten hair and scalp with warm water sufficiently and massage the scalp with 3~5ml.-Apply a proper amount to foam and apply to the hair and scalp sufficiently.-Massage for about 3 minutes and rinse.

WARNINGS

1. Do not use in the following cases(Eczema and scalp wounds)
2.Side Effects
1)Due to the use of this druf if rash, irritation, itching and symptopms of hypersnesitivity occur dicontinue use and consult your phamacisr or doctor
3.General Precautions
1)If in contact with the eyes, wash out thoroughty with water If the symptoms are servere, seek medical advice immediately
2)This product is for exeternal use only. Do not use for internal use
4.Storage and handling precautions
1)If possible, avoid direct sunlight and store in cool and area of low humidity
2)In order to maintain the quality of the product and avoid misuse
3)Avoid placing the product near fire and store out in reach of children

DOSAGE AND ADMINISTRATION

for external use only